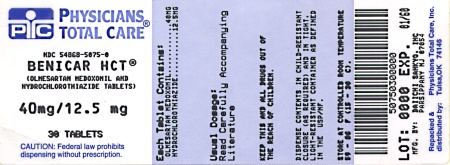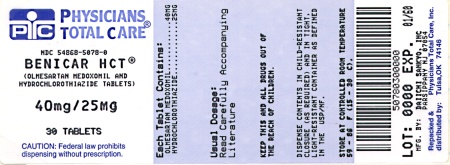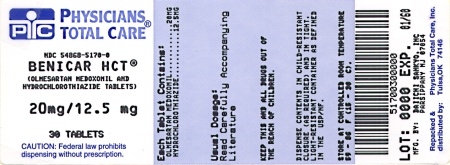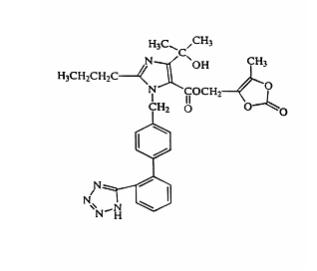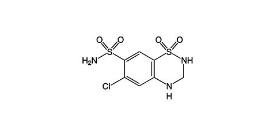 DRUG LABEL: Benicar Hct
NDC: 54868-5170 | Form: TABLET, FILM COATED
Manufacturer: Physicians Total Care, Inc.
Category: prescription | Type: HUMAN PRESCRIPTION DRUG LABEL
Date: 20101130

ACTIVE INGREDIENTS: OLMESARTAN MEDOXOMIL 20 mg/1 1; HYDROCHLOROTHIAZIDE 12.5 mg/1 1
INACTIVE INGREDIENTS: HYDROXYPROPYL CELLULOSE; HYPROMELLOSES; LACTOSE; HYDROXYPROPYL CELLULOSE, LOW SUBSTITUTED; MAGNESIUM STEARATE; CELLULOSE, MICROCRYSTALLINE; FERRIC OXIDE RED; TALC; TITANIUM DIOXIDE; FERRIC OXIDE YELLOW

BOXED WARNING

USE IN PREGNANCY

When used in pregnancy during the second and third trimesters, drugs that act directly on the renin-angiotensin system can cause injury and even death to the developing fetus.When pregnancy is detected, BENICAR HCT® should be discontinued as soon as possible. See WARNINGS, Fetal/Neonatal Morbidity and Mortality.

DESCRIPTION

BENICAR HCT® (olmesartan medoxomil-hydrochlorothiazide) is a combination of an angiotensin II receptor antagonist (AT1 subtype), olmesartan medoxomil, and a thiazide diuretic, hydrochlorothiazide (HCTZ).

Olmesartan medoxomil, a prodrug, is hydrolyzed to olmesartan during absorption from the gastrointestinal tract.

Olmesartan medoxomil is 2,3-dihydroxy-2-butenyl 4-(1-hydroxy-1-methylethyl)-2-propyl-1-[p-(o-1H-tetrazol-5-ylphenyl)benzyl]imidazole-5-carboxylate, cyclic 2,3-carbonate.

Its empirical formula is C29H30N6O6 and its structural formula is:

Olmesartan medoxomil is a white to light yellowish-white powder or crystalline powder with a molecular weight of 558.6. It is practically insoluble in water and sparingly soluble in methanol.

Hydrochlorothiazide is 6-chloro-3,4-dihydro-2H-1,2,4-benzo-thiadiazine-7-sulfonamide 1,1-dioxide. Its empirical formula is C7H8ClN3O4S2 and its structural formula is:

Hydrochlorothiazide is a white, or practically white, crystalline powder with a molecular weight of 297.7. Hydrochlorothiazide is slightly soluble in water but freely soluble in sodium hydroxide solution.

BENICAR HCT® is available for oral administration in tablets containing 20 mg or 40 mg of olmesartan medoxomil combined with 12.5 mg of hydrochlorothiazide, or 40 mg of olmesartan medoxomil combined with 25 mg of hydrochlorothiazide. Inactive ingredients include: hydroxypropylcellulose, hypromellose, lactose, low-substituted hydroxypropylcellulose, magnesium stearate, microcrystalline cellulose, red iron oxide, talc, titanium dioxide and yellow iron oxide.

CLINICAL PHARMACOLOGY

Mechanism of Action Olmesartan medoxomil

Angiotensin II is formed from angiotensin I in a reaction catalyzed by angiotensin converting enzyme (ACE, kininase II). Angiotensin II is the principal pressor agent of the renin-angiotensin system, with effects that include vasoconstriction, stimulation of synthesis and release of aldosterone, cardiac stimulation and renal reabsorption of sodium. Olmesartan blocks the vasoconstrictor effects of angiotensin II by selectively blocking the binding of angiotensin II to the AT1 receptor in vascular smooth muscle. Its action is, therefore, independent of the pathways for angiotensin II synthesis.

An AT2 receptor is found also in many tissues, but this receptor is not known to be associated with cardiovascular homeostasis. Olmesartan has more than a 12,500-fold greater affinity for the AT1 receptor than for the AT2 receptor.

Blockade of the renin-angiotensin system with ACE inhibitors, which inhibit the biosynthesis of angiotensin II from angiotensin I, is a mechanism of many drugs used to treat hypertension. ACE inhibitors also inhibit the degradation of bradykinin, a reaction also catalyzed by ACE. Because olmesartan medoxomil does not inhibit ACE (kininase II), it does not affect the response to bradykinin. Whether this difference has clinical relevance is not yet known.

Blockade of the angiotensin II receptor inhibits the negative regulatory feedback of angiotensin II on renin secretion, but the resulting increased plasma renin activity and circulating angiotensin II levels do not overcome the effect of olmesartan on blood pressure.

Hydrochlorothiazide

Hydrochlorothiazide is a thiazide diuretic. Thiazides affect the renal tubular mechanisms of electrolyte reabsorption, directly increasing excretion of sodium and chloride in approximately equivalent amounts. Indirectly, the diuretic action of hydrochlorothiazide reduces plasma volume, with consequent increases in plasma renin activity, increases in aldosterone secretion, increases in urinary potassium loss, and decreases in serum potassium. The renin-aldosterone link is mediated by angiotensin II, so co-administration of an angiotensin II receptor antagonist tends to reverse the potassium loss associated with these diuretics.

The mechanism of the antihypertensive effect of thiazides is not fully understood.

Pharmacokinetics General Olmesartan medoxomil

Olmesartan medoxomil is rapidly and completely bioactivated by ester hydrolysis to olmesartan during absorption from the gastrointestinal tract. Olmesartan appears to be eliminated in a biphasic manner with a terminal elimination half-life of approximately 13 hours. Olmesartan shows linear pharmacokinetics following single oral doses of up to 320 mg and multiple oral doses of up to 80 mg. Steady-state levels of olmesartan are achieved within 3 to 5 days and no accumulation in plasma occurs with once-daily dosing.

The absolute bioavailability of olmesartan is approximately 26%. After oral administration, the peak plasma concentration (Cmax) of olmesartan is reached after 1 to 2 hours. Food does not affect the bioavailability of olmesartan.

Hydrochlorothiazide

When plasma levels have been followed for at least 24 hours, the plasma half-life has been observed to vary between 5.6 and 14.8 hours.

Metabolism and Excretion Olmesartan medoxomil

Following the rapid and complete conversion of olmesartan medoxomil to olmesartan during absorption, there is virtually no further metabolism of olmesartan. Total plasma clearance of olmesartan is 1.3 L/h, with a renal clearance of 0.6 L/h. Approximately 35% to 50% of the absorbed dose is recovered in urine while the remainder is eliminated in feces via the bile.

Hydrochlorothiazide

Hydrochlorothiazide is not metabolized but is eliminated rapidly by the kidney. At least 61% of the oral dose is eliminated unchanged within 24 hours.

Distribution Olmesartan

The volume of distribution of olmesartan is approximately 17 L. Olmesartan is highly bound to plasma proteins (99%) and does not penetrate red blood cells. The protein binding is constant at plasma olmesartan concentrations well above the range achieved with recommended doses.

In rats, olmesartan crossed the blood-brain barrier poorly, if at all. Olmesartan passed across the placental barrier in rats and was distributed to the fetus. Olmesartan was distributed to milk at low levels in rats.

Hydrochlorothiazide

Hydrochlorothiazide crosses the placental but not the blood-brain barrier and is excreted in breast milk.

Special Populations

Pediatric:The pharmacokinetics of olmesartan have not been investigated in patients <18 years of age.

Geriatric:The pharmacokinetics of olmesartan were studied in the elderly (>65 years). Overall, maximum plasma concentrations of olmesartan were similar in young adults and the elderly. Modest accumulation of olmesartan was observed in the elderly with repeated dosing; AUCss,τ was 33% higher in elderly patients, corresponding to an approximate 30% reduction in CLR.

Gender:Minor differences were observed in the pharmacokinetics of olmesartan in women compared to men. AUC and Cmax were 10-15% higher in women than in men.

Renal Insufficiency:In patients with renal insufficiency, serum concentrations of olmesartan were elevated compared to subjects with normal renal function. After repeated dosing, the AUC was approximately tripled in patients with severe renal impairment (creatinine clearance <20 mL/min). The pharmacokinetics of olmesartan in patients undergoing hemodialysis has not been studied.

Hepatic Insufficiency:Increases in AUC0-∞ and Cmax for olmesartan were observed in patients with moderate hepatic impairment compared to those in matched controls, with an increase in AUC of about 60%.

Drug Interactions

See PRECAUTIONS, Drug Interactions.

Pharmacodynamics Olmesartan medoxomil

Olmesartan medoxomil doses of 2.5 to 40 mg inhibit the pressor effects of angiotensin I infusion. The duration of the inhibitory effect was related to dose, with doses of olmesartan medoxomil >40 mg giving >90% inhibition at 24 hours.

Plasma concentrations of angiotensin I and angiotensin II and plasma renin activity (PRA) increase after single and repeated administration of olmesartan medoxomil to healthy subjects and hypertensive patients. Repeated administration of up to 80 mg olmesartan medoxomil had minimal influence on aldosterone levels and no effect on serum potassium.

Hydrochlorothiazide

After oral administration of hydrochlorothiazide, diuresis begins within 2 hours, peaks in about 4 hours and lasts about 6 to 12 hours.

Clinical Trials Olmesartan medoxomil

The antihypertensive effects of olmesartan medoxomil have been demonstrated in seven placebo-controlled studies at doses ranging from 2.5 to 80 mg for 6 to 12 weeks, each showing statistically significant reductions in peak and trough blood pressure. A total of 2693 patients (2145 olmesartan medoxomil; 548 placebo) with essential hypertension were studied. Olmesartan medoxomil once daily (QD) lowered diastolic and systolic blood pressure. The response was dose-related. An olmesartan medoxomil dose of 20 mg daily produces a trough sitting BP reduction over placebo of about 10/6 mm Hg and a dose of 40 mg daily produces a trough sitting BP reduction over placebo of about 12/7 mm Hg. Olmesartan medoxomil doses greater than 40 mg had little additional effect. The onset of the antihypertensive effect occurred within 1 week and was largely manifest after 2 weeks.

The blood pressure lowering effect was maintained throughout the 24-hour period with olmesartan medoxomil once daily, with trough-to-peak ratios for systolic and diastolic response between 60 and 80%.

The blood pressure lowering effect of olmesartan medoxomil, with and without hydrochlorothiazide, was maintained in patients treated for up to 1 year. There was no evidence of tachyphylaxis during long-term treatment with olmesartan medoxomil or rebound effect following abrupt withdrawal of olmesartan medoxomil after 1 year of treatment.

The antihypertensive effect of olmesartan medoxomil was similar in men and women and in patients older and younger than 65 years. The effect was smaller in black patients (usually a low-renin population), as has been seen with other ACE inhibitors, angiotensin receptor blockers and beta-blockers. Olmesartan medoxomil had an additional blood pressure lowering effect when added to hydrochlorothiazide.

Olmesartan medoxomil-hydrochlorothiazide

In clinical trials 1230 patients were exposed to the combination of olmesartan medoxomil (2.5 mg to 40 mg) and hydrochlorothiazide (12.5 mg to 25 mg). These trials included one placebo-controlled factorial trial (n=502) in mild-moderate hypertensives with combinations of olmesartan medoxomil (10 mg, 20 mg, 40 mg or placebo) and hydrochlorothiazide (12.5 mg, 25 mg or placebo). The antihypertensive effect of the combination on trough blood pressure was related to the dose of each component (see table below).

Placebo-Adjusted Changes in Sitting Systolic/Diastolic Blood Pressure (mmHg)
 | Olmesartan Medoxomil dose
HCTZ dose | 0 mg | 10 mg | 20 mg | 40 mg
0 mg | -- | 7/5 | 12/5 | 13/7
12.5 mg | 5/1 | 17/8 | 17/8 | 16/10
25 mg | 14/5 | 19/11 | 22/11 | 24/14

Once-daily dosing with 20 mg olmesartan medoxomil and 12.5 mg hydrochlorothiazide, 40 mg olmesartan medoxomil and 12.5 mg hydrochlorothiazide or 40 mg olmesartan medoxomil and 25 mg hydrochlorothiazide produced mean placebo-adjusted blood pressure reductions at trough (24 hours post-dosing) ranging from 17/8 to 24/14 mm Hg.

The onset of the antihypertensive effect occurred within 1 week and was near maximal at 4 weeks. The antihypertensive effect was independent of gender, but there were too few subjects to identify response differences based on race or age greater than or less than 65 years. No appreciable changes in trough heart rate were observed with combination therapy in the placebo-controlled trial.

INDICATIONS AND USAGE

BENICAR HCT® is indicated for the treatment of hypertension. This fixed dose combination is not indicated for initial therapy (see DOSAGE AND ADMINISTRATION).

CONTRAINDICATIONS

BENICAR HCT® is contraindicated in patients who are hypersensitive to any component of this product.

Because of the hydrochlorothiazide component, this product is contraindicated in patients with anuria or hypersensitivity to other sulfonamide-derived drugs.

WARNINGS

Fetal/Neonatal Morbidity and Mortality

Drugs that act directly on the renin-angiotensin system can cause fetal and neonatal morbidity and death when administered to pregnant women. Several dozen cases have been reported in the world literature of patients who were taking angiotensin converting enzyme inhibitors. When pregnancy is detected, BENICAR HCT® should be discontinued as soon as possible.

The use of drugs that act directly on the renin-angiotensin system during the second and third trimesters of pregnancy has been associated with fetal and neonatal injury, including hypotension, neonatal skull hypoplasia, anuria, reversible or irreversible renal failure and death. Oligohydramnios has also been reported, presumably resulting from decreased fetal function; oligohydramnios in this setting has been associated with fetal limb contractures, craniofacial deformation and hypoplastic lung development. Prematurity, intrauterine growth retardation and patent ductus arteriosus have also been reported, although it is not clear whether these occurrences were due to exposure to the drug.

These adverse effects do not appear to have resulted from intrauterine drug exposure that has been limited to the first trimester. Mothers whose embryos and fetuses are exposed to an angiotensin II receptor antagonist only during the first trimester should be so informed. Nonetheless, when patients become pregnant, physicians should have the patient discontinue the use of BENICAR HCT® as soon as possible.

Rarely (probably less often than once in every thousand pregnancies), no alternative to a drug acting on the renin-angiotensin system will be found. In these rare cases, the mothers should be apprised of the potential hazards to their fetuses and serial ultrasound examinations should be performed to assess the intra-amniotic environment.

If oligohydramnios is observed, BENICAR HCT® should be discontinued unless it is considered life-saving for the mother. Contraction stress testing (CST), a nonstress test (NST) or biophysical profiling (BPP) may be appropriate, depending upon the week of pregnancy. Patients and physicians should be aware, however, that oligohydramnios may not appear until after the fetus has sustained irreversible injury.

Infants with histories of in utero exposure to an angiotensin II receptor antagonist should be closely observed for hypotension, oliguria and hyperkalemia. If oliguria occurs, attention should be directed toward support of blood pressure and renal perfusion. Exchange transfusion or dialysis may be required as means of reversing hypotension and/or substituting for disordered renal function.

There is no clinical experience with the use of BENICAR HCT® in pregnant women. No teratogenic effects were observed when 1.6:1 combinations of olmesartan medoxomil and hydrochlorothiazide were administered to pregnant mice at oral doses up to 1625 mg/kg/day (122 times the maximum recommended human dose [MRHD] on a mg/m^2 basis) or pregnant rats at oral doses up to 1625 mg/kg/day (280 times the MRHD on a mg/m^2 basis). In rats, however, fetal body weights at 1625 mg/kg/day (a toxic, sometimes lethal dose in the dams) were significantly lower than control. The no observed effect dose for developmental toxicity in rats, 162.5 mg/kg/day, is about 28 times, on a mg/m^2 basis, the MRHD of BENICAR HCT® (40 mg olmesartan medoxomil /25 mg hydrochlorothiazide/day).

Thiazides cross the placental barrier and appear in cord blood. There is a risk of fetal or neonatal jaundice, thrombocytopenia and possibly other adverse reactions that have occurred in adults.

Hypotension in Volume- or Salt-Depleted Patients

In patients with an activated renin-angiotensin system, such as volume- or salt-depleted patients (e.g., those being treated with high doses of diuretics), symptomatic hypotension may occur after initiation of treatment with BENICAR HCT®, as with any angiotensin receptor blocker. Treatment should start under close medical supervision. If hypotension does occur, the patient should be placed in the supine position and, if necessary, given an intravenous infusion of normal saline (See DOSAGE AND ADMINISTRATION). When electrolyte and fluid imbalances have been corrected, therapy usually can be continued without difficulty. A transient hypotensive response is not a contraindication to further treatment.

Hydrochlorothiazide Hepatic Impairment

Thiazides should be used with caution in patients with impaired hepatic function or progressive liver disease, since minor alterations of fluid and electrolyte balance may precipitate hepatic coma.

Hypersensitivity Reaction

Hypersensitivity reactions to hydrochlorothiazide may occur in patients with or without a history of allergy or bronchial asthma, but are more likely in patients with such a history.

Systemic Lupus Erythematosus

Thiazide diuretics have been reported to cause exacerbation or activation of systemic lupus erythematosus.

Lithium Interaction

Lithium generally should not be given with thiazides (see PRECAUTIONS: Drug Interactions; Hydrochlorothiazide, Lithium).

PRECAUTIONS

General Olmesartan medoxomil-hydrochlorothiazide

In a double-blind clinical trial of various doses of olmesartan medoxomil and hydrochlorothiazide, the incidence of hypertensive patients who developed hypokalemia (serum potassium <3.4 mEq/L) was 2.1%; the incidence of hyperkalemia (serum potassium >5.7 mEq/L) was 0.4%. In this trial, no patient discontinued due to increases or decreases in serum potassium.

Hydrochlorothiazide

Periodic determinations of serum electrolytes to detect possible electrolyte imbalance should be performed at appropriate intervals. All patients receiving thiazide therapy should be observed for clinical signs of fluid or electrolyte imbalance: hyponatremia, hypochloremic alkalosis and hypokalemia. Serum and urine electrolyte determinations are important when the patient is vomiting excessively or receiving parenteral fluids. Warning signs or symptoms of fluid and electrolyte imbalance, irrespective of cause, include dryness of mouth, thirst, weakness, lethargy, drowsiness, restlessness, confusion, seizures, muscle pains or cramps, muscular fatigue, hypotension, oliguria, tachycardia and gastrointestinal disturbances such as nausea and vomiting.

Hypokalemia may develop, especially with brisk diuresis, when severe cirrhosis is present, or after prolonged therapy.

Interference with adequate oral electrolyte intake will also contribute to hypokalemia. Hypokalemia may cause cardiac arrhythmia and may also sensitize or exaggerate the response of the heart to the toxic effects of digitalis (e.g., increased ventricular irritability).

Although any chloride deficit is generally mild and usually does not require specific treatment except under extraordinary circumstances (as in liver disease or renal disease), chloride replacement may be required in the treatment of metabolic alkalosis.

Dilutional hyponatremia may occur in edematous patients in hot weather; appropriate therapy is water restriction, rather than administration of salt except in rare instances when the hyponatremia is life-threatening. In actual salt depletion, appropriate replacement is the therapy of choice.

Hyperuricemia may occur or frank gout may be precipitated in certain patients receiving thiazide therapy.

In diabetic patients dosage adjustments of insulin or oral hypoglycemic agents may be required. Hyperglycemia may occur with thiazide diuretics. Thus latent diabetes mellitus may become manifest during thiazide therapy.

The antihypertensive effects of the drug may be enhanced in the post-sympathectomy patient.

If progressive renal impairment becomes evident consider withholding or discontinuing diuretic therapy.

Thiazides have been shown to increase the urinary excretion of magnesium; this may result in hypomagnesemia.

Thiazides may decrease urinary calcium excretion. Thiazides may cause intermittent and slight elevation of serum calcium in the absence of known disorders of calcium metabolism. Marked hypercalcemia may be evidence of hyperparathyroidism. Thiazides should be discontinued before carrying out tests for parathyroid function.

Increases in cholesterol and triglyceride levels may be associated with thiazide diuretic therapy.

Impaired Renal Function

As a consequence of inhibiting the renin-angiotensin-aldosterone system, changes in renal function may be anticipated in susceptible individuals treated with olmesartan medoxomil. In patients whose renal function may depend upon the activity of the renin-angiotensin-aldosterone system (e.g. patients with severe congestive heart failure), treatment with angiotensin converting enzyme inhibitors and angiotensin receptor antagonists has been associated with oliguria and/or progressive azotemia and (rarely) with acute renal failure and/or death. Similar results may be anticipated in patients treated with olmesartan medoxomil. (See CLINICAL PHARMACOLOGY, Special Populations)

In studies of ACE inhibitors in patients with unilateral or bilateral renal artery stenosis, increases in serum creatinine or blood urea nitrogen (BUN) have been reported. There has been no long-term use of olmesartan medoxomil in patients with unilateral or bilateral renal artery stenosis, but similar results may be expected.

Thiazides should be used with caution in severe renal disease. In patients with renal disease, thiazides may precipitate azotemia. Cumulative effects of the drug may develop in patients with impaired renal function.

Information for Patients

Pregnancy:Female patients of childbearing age should be told about the consequences of second and third trimester exposure to drugs that act on the renin-angiotensin system and they should be told also that these consequences do not appear to have resulted from intrauterine drug exposure that has been limited to the first trimester. These patients should be asked to report pregnancies to their physicians as soon as possible.

Symptomatic Hypotension:A patient receiving BENICAR HCT® should be cautioned that lightheadedness can occur, especially during the first days of therapy, and that it should be reported to the prescribing physician. The patients should be told that if syncope occurs, BENICAR HCT® should be discontinued until the physician has been consulted.

All patients should be cautioned that inadequate fluid intake, excessive perspiration, diarrhea or vomiting can lead to an excessive fall in blood pressure, with the same consequences of light-headedness and possible syncope.

Drug Interactions Olmesartan medoxomil

No significant drug interactions were reported in studies in which olmesartan medoxomil was co-administered with hydrochlorothiazide, digoxin or warfarin in healthy volunteers. The bioavailability of olmesartan was not significantly altered by the co-administration of antacids [Al(OH)3/Mg(OH)2]. Olmesartan medoxomil is not metabolized by the cytochrome P450 system and has no effects on P450 enzymes; thus, interactions with drugs that inhibit, induce or are metabolized by those enzymes are not expected.

Hydrochlorothiazide

When administered concurrently the following drugs may interact with thiazide diuretics:

Alcohol, Barbiturates, Or Narcotics– potentiation of orthostatic hypotension may occur.

Antidiabetic Drugs (oral agents and insulin)– dosage adjustment of the antidiabetic drug may be required.

Other Antihypertensive Drugs– additive effect or potentiation.

Cholestyramine and Colestipol Resins– absorption of hydrochlorothiazide is impaired in the presence of anionic exchange resins. Single doses of either cholestyramine or colestipol resins bind the hydrochlorothiazide and reduce its absorption from the gastrointestinal tract by up to 85 and 43 percent, respectively.

Corticosteroids, ACTH– intensified electrolyte depletion, particularly hypokalemia.

Pressor Amines (e.g. Norepinephrine)– possible decreased response to pressor amines but not sufficient to preclude their use.

Skeletal Muscle Relaxants, Non depolarizing (e.g. Tubocurarine)– possible increased responsiveness to the muscle relaxant.

Lithium– should not generally be given with diuretics. Diuretic agents reduce the renal clearance of lithium and add a high risk of lithium toxicity. Refer to the package insert for lithium preparations before use of such preparation with olmesartan medoxomil-hydrochlorothiazide.

Non-steroidal Anti-inflammatory Drugs– in some patients the administration of a non-steroidal anti-inflammatory agent can reduce the diuretic, natriuretic and antihypertensive effects of loop, potassium-sparing and thiazide diuretics. Therefore, when olmesartan medoxomil-hydrochlorothiazide tablets and non-steroidal anti-inflammatory agents are used concomitantly, the patients should be observed closely to determine if the desired effect of the diuretic is obtained.

Carcinogenesis, Mutagenesis, Impairment of Fertility Olmesartan medoxomil-hydrochlorothiazide

No carcinogenicity studies with olmesartan medoxomil-hydrochlorothiazide have been conducted.

Olmesartan medoxomil-hydrochlorothiazide in a ratio of 20:12.5 was negative in the Salmonella-Escherichia coli/mammalian microsome reverse mutation test up to the maximum recommended plate concentration for the standard assays. Olmesartan medoxomil and hydrochlorothiazide were tested individually and in combination ratios of 40:12.5, 20:12.5 and 10:12.5, for clastogenic activity in the in vitro Chinese hamster lung (CHL) chromosomal aberration assay. A positive response was seen for each component and combination ratio. However, no synergism in clastogenic activity was detected between olmesartan medoxomil and hydrochlorothiazide at any combination ratio. Olmesartan medoxomil-hydrochlorothiazide in a ratio of 20:12.5, administered orally, tested negative in the in vivo mouse bone marrow erythrocyte micronucleus assay at administered doses of up to 3144 mg/kg.

No studies of impairment of fertility with olmesartan medoxomil-hydrochlorothiazide have been conducted.

Olmesartan medoxomil

Olmesartan medoxomil was not carcinogenic when administered by dietary administration to rats for up to 2 years. The highest dose tested (2000 mg/kg/day) was, on a mg/m^2 basis, about 480 times the maximum recommended human dose (MRHD) of 40 mg/day. Two carcinogenicity studies conducted in mice, a 6-month gavage study in the p53 knockout mouse and a 6-month dietary administration study in the Hras2 transgenic mouse, at doses of up to 1000 mg/kg/day (about 120 times the MRHD), revealed no evidence of a carcinogenic effect of olmesartan medoxomil.

Both olmesartan medoxomil and olmesartan tested negative in the in vitro Syrian hamster embryo cell transformation assay and showed no evidence of genetic toxicity in the Ames (bacterial mutagenicity) test. However, both were shown to induce chromosomal aberrations in cultured cells in vitro (Chinese hamster lung) and both tested positive for thymidine kinase mutations in the in vitro mouse lymphoma assay. Olmesartan medoxomil tested negative in vivo for mutations in the MutaMouse intestine and kidney, and for clastogenicity in mouse bone marrow (micronucleus test) at oral doses of up to 2000 mg/kg (olmesartan not tested).

Fertility of rats was unaffected by administration of olmesartan medoxomil at dose levels as high as 1000 mg/kg/day (240 times the MRHD) in a study in which dosing was begun 2 (female) or 9 (male) weeks prior to mating.

Hydrochlorothiazide

Two-year feeding studies in mice and rats conducted under the auspices of the National Toxicology Program (NTP) uncovered no evidence of a carcinogenic potential of hydrochlorothiazide in female mice (at doses of up to approximately 600 mg/kg/day) or in male and female rats (at doses of up to approximately 100 mg/kg/day). The NTP, however, found equivocal evidence for hepatocarcinogenicity in male mice.

Hydrochlorothiazide was not genotoxic in vitro in the Ames mutagenicity assay of Salmonella typhimurium strains TA 98, TA 100, TA 1535, TA 1537 and TA 1538, or in the Chinese Hamster Ovary (CHO) test for chromosomal aberrations. It was also not genotoxic in vivo in assays using mouse germinal cell chromosomes, Chinese hamster bone marrow chromosomes, or the Drosophila sex-linked recessive lethal trait gene. Positive test results were obtained in the in vitro CHO Sister Chromatid Exchange (clastogenicity) assay, the Mouse Lymphoma Cell (mutagenicity) assay and the Aspergillus nidulans non-disjunction assay.

Hydrochlorothiazide had no adverse effects on the fertility of mice and rats of either sex in studies wherein these species were exposed, via their diet, to doses of up to 100 and 4 mg/kg, respectively, prior to mating and throughout gestation.

Pregnancy

Pregnancy Categories C (first trimester) and D (second and third trimesters)

(See WARNINGS:Fetal/Neonatal Morbidity and Mortality)

Nursing Mothers

It is not known whether olmesartan is excreted in human milk, but olmesartan is secreted at low concentration in the milk of lactating rats. Because of the potential for adverse effects on the nursing infant, a decision should be made whether to discontinue nursing or discontinue the drug, taking into account the importance of the drug to the mother.

Thiazides appear in human milk. Because of the potential for adverse effects on the nursing infant, a decision should be made whether to discontinue nursing or discontinue the drug, taking into account the importance of the drug to the mother.

Pediatric Use

Safety and effectiveness in pediatric patients have not been established.

Geriatric Use

Clinical studies of BENICAR HCT® did not include sufficient numbers of subjects aged 65 and over to determine whether they respond differently from younger subjects. Other reported clinical experience has not identified differences in responses between the elderly and younger patients. In general, dose selection for an elderly patient should be cautious, usually starting at the low end of the dosing range, reflecting the greater frequency of decreased hepatic, renal or cardiac function and of concomitant diseases or other drug therapy.

Olmesartan and hydrochlorothiazide are substantially excreted by the kidney, and the risk of toxic reactions to this drug may be greater in patients with impaired renal function.

ADVERSE REACTIONS

Olmesartan medoxomil-hydrochlorothiazide

Olmesartan medoxomil-hydrochlorothiazide has been evaluated for safety in 1243 hypertensive patients. Treatment with olmesartan medoxomil-hydrochlorothiazide was well tolerated, with an incidence of adverse events similar to placebo. Events generally were mild, transient and had no relationship to the dose of olmesartan medoxomil-hydrochlorothiazide.

In the clinical trials, the overall frequency of adverse events was not dose-related. Analysis of gender, age and race groups demonstrated no differences between olmesartan medoxomil-hydrochlorothiazide and placebo-treated patients. The rate of withdrawals due to adverse events in all trials of hypertensive patients was 2.0% (25/1243) of patients treated with olmesartan medoxomil-hydrochlorothiazide and 2.0% (7/342) of patients treated with placebo.

In a placebo-controlled clinical trial, the following adverse events reported with olmesartan medoxomil-hydrochlorothiazide occurred in >2% of patients, and more often on the olmesartan medoxomil-hydrochlorothiazide combination than on placebo, regardless of drug relationship:

 | Olmesartan/HCTZ (N=247) (%) | Placebo (N=42) (%) | Olmesartan (N=125) (%) | HCTZ (N=88) (%)
Gastrointestinal
Nausea | 3 | 0 | 2 | 1
Metabolic
Hyperuricemia | 4 | 2 | 0 | 2
Nervous System
Dizziness | 9 | 2 | 1 | 8
Respiratory
Upper Respiratory Tract Infection | 7 | 0 | 6 | 7

The following adverse events were also reported at a rate of >2%, but were as, or more, common in the placebo group: headache and urinary tract infection.

Other adverse events that have been reported with an incidence of greater than 1.0%, whether or not attributed to treatment, in the more than 1200 hypertensive patients treated with olmesartan medoxomil-hydrochlorothiazide in controlled or open-label trials are listed below.

Body as a Whole:chest pain, back pain, peripheral edema
Central and Peripheral Nervous System: vertigo
Gastrointestinal: abdominal pain, dyspepsia, gastroenteritis, diarrhea
Liver and Biliary System: SGOT increased, GGT increased, SGPT increased
Metabolic and Nutritional: hyperlipemia, creatine phosphokinase increased, hyperglycemia
Musculoskeletal: arthritis, arthralgia, myalgia
Respiratory System: coughing
Skin and Appendages Disorders: rash
Urinary System: hematuria

Facial edema was reported in 2/1243 patients receiving olmesartan medoxomil-hydrochlorothiazide. Angioedema has been reported with angiotensin II receptor antagonists.

Olmesartan medoxomil

Other adverse events that have been reported with an incidence of greater than 0.5%, whether or not attributed to treatment, in more than 3100 hypertensive patients treated with olmesartan medoxomil monotherapy in controlled or open-label trials are tachycardia and hypercholesterolemia.

Hydrochlorothiazide

Other adverse experiences that have been reported with hydrochlorothiazide, without regard to causality, are listed below:

Body as a Whole:weakness
Digestive: pancreatitis, jaundice (intrahepatic cholestatic jaundice), sialadenitis, cramping, gastric irritation
Hematologic: aplastic anemia, agranulocytosis, leukopenia, hemolytic anemia, thrombocytopenia
Hypersensitivity: purpura, photosensitivity, urticaria, necrotizing angiitis (vasculitis and cutaneous vasculitis), fever, respiratory distress including pneumonitis and pulmonary edema, anaphylactic reactions
Metabolic: hyperglycemia, glycosuria, hyperuricemia
Musculoskeletal: muscle spasm
Nervous System/Psychiatric: restlessness
Renal: renal failure, renal dysfunction, interstitial nephritis
Skin: erythema multiforme including Stevens-Johnson syndrome, exfoliative dermatitis including toxic epidermal necrolysis
Special Senses: transient blurred vision, xanthopsia

Laboratory Test Findings

In controlled clinical trials, clinically important changes in standard laboratory parameters were rarely associated with administration of olmesartan medoxomil-hydrochlorothiazide.

Creatinine, Blood Urea Nitrogen:Increases in blood urea nitrogen (BUN) and serum creatinine of >50% were observed in 1.3% of patients. No patients were discontinued from clinical trials of olmesartan medoxomil-hydrochlorothiazide due to increased BUN or creatinine.

Hemoglobin and Hematocrit:A greater than 20% decrease in hemoglobin and hematocrit was observed in 0.0 % and 0.4% (one patient), respectively, of olmesartan medoxomil-hydrochlorothiazide patients, compared with 0.0% and 0.0%, respectively, in placebo-treated patients. No patients were discontinued due to anemia.

Post-Marketing Experience: The following adverse reactions have been reported in post-marketing experience:

Body as a Whole:Asthenia, angioedema
Gastrointestinal: Vomiting
Metabolic and Nutritional Disorders: Hyperkalemia
Musculoskeletal: Rhabdomyolysis
Urogenital System: Acute renal failure, increased blood creatinine levels
Skin and Appendages: Alopecia, pruritus, urticaria

OVERDOSAGE

Olmesartan medoxomil

Limited data are available related to overdosage in humans. The most likely manifestations of overdosage would be hypotension and tachycardia; bradycardia could be encountered if parasympathetic (vagal) stimulation occurs. If symptomatic hypotension should occur, supportive treatment should be initiated. The dialyzability of olmesartan is unknown.

No lethality was observed in acute toxicity studies in mice and rats given single oral doses up to 2000 mg/kg olmesartan medoxomil. The minimum lethal oral dose of olmesartan medoxomil in dogs was greater than 1500 mg/kg.

Hydrochlorothiazide

The most common signs and symptoms of overdose observed in humans are those caused by electrolyte depletion (hypokalemia, hypochloremia, hyponatremia) and dehydration resulting from excessive diuresis. If digitalis has also been administered, hypokalemia may accentuate cardiac arrhythmias. The degree to which hydrochlorothiazide is removed by hemodialysis has not been established. The oral LD50 of hydrochlorothiazide is greater than 10 g/kg in both mice and rats.

DOSAGE AND ADMINISTRATION

The usual recommended starting dose of BENICAR® (olmesartan medoxomil) is 20 mg once daily when used as monotherapy in patients who are not volume-contracted. For patients requiring further reduction in blood pressure after 2 weeks of therapy, the dose may be increased to 40 mg. Doses above 40 mg do not appear to have greater effect. Twice-daily dosing offers no advantage over the same total dose given once daily. No initial dosage adjustment is recommended for elderly patients, for patients with moderate to marked renal impairment (creatinine clearance <40mL/min) or with moderate to marked hepatic dysfunction (see CLINICAL PHARMACOLOGY, Special Populations). For patients with possible depletion of intravascular volume (e.g., patients treated with diuretics, particularly those with impaired renal function), BENICAR® should be initiated under close medical supervision and consideration should be given to use of a lower starting dose (see WARNINGS, Hypotension in Volume- or Salt-Depleted Patients).

Hydrochlorothiazide is effective in doses between 12.5 mg and 50 mg once daily.

The side effects (see WARNINGS) of BENICAR® are generally rare and independent of dose; those of hydrochlorothiazide are most typically dose-dependent (primarily hypokalemia). Some dose-independent phenomena (e.g., pancreatitis) do occur with hydrochlorothiazide. Therapy with any combination of olmesartan medoxomil and hydrochlorothiazide will be associated with both sets of dose-independent side effects.

To minimize dose-independent side effects, it is usually appropriate to begin combination therapy only after a patient has failed to achieve the desired effect with monotherapy.

Replacement Therapy

BENICAR HCT® (olmesartan medoxomil-hydrochlorothiazide) may be substituted for its titrated components.

Dose Titration by Clinical Effect

BENICAR HCT® is available in strengths of 20 mg/12.5 mg, 40 mg/12.5 mg and 40 mg/25 mg. A patient whose blood pressure is inadequately controlled by BENICAR® or hydrochlorothiazide alone may be switched to once daily BENICAR HCT® (olmesartan medoxomil-hydrochlorothiazide).

Dosing should be individualized. Depending on the blood pressure response, the dose may be titrated at intervals of 2-4 weeks.

If blood pressure is not controlled by BENICAR® alone, hydrochlorothiazide may be added starting with a dose of 12.5 mg and later titrated to 25 mg once daily.

If a patient is taking hydrochlorothiazide, BENICAR® may be added starting with a dose of 20 mg once daily and titrated to 40 mg, for inadequate blood pressure control. If large doses of hydrochlorothiazide have been used as monotherapy and volume depletion or hyponatremia is present, caution should be used when adding BENICAR® or switching to BENICAR HCT® as marked decreases in blood pressure may occur (see WARNINGS, Hypotension in Volume- or Salt-Depleted Patients). Consideration should be given to reducing the dose of hydrochlorothiazide to 12.5 mg before adding BENICAR®. The antihypertensive effect of BENICAR HCT® is related to the dose of both components over the range of 10 mg/12.5 mg to 40 mg/25 mg (see CLINICAL PHARMACOLOGY, Clinical Trials). The dose of BENICAR HCT® is one tablet once daily. More than one tablet daily is not recommended.

BENICAR HCT® may be administered with other antihypertensive agents.

Patients with Renal Impairment

The usual regimens of therapy with BENICAR HCT® may be followed provided the patient’s creatinine clearance is >30 mL/min. In patients with more severe renal impairment, loop diuretics are preferred to thiazides, so BENICAR HCT® is not recommended.

Patients with Hepatic Impairment

No dosage adjustment is necessary with hepatic impairment (see CLINICAL PHARMACOLOGY, Special Populations).

HOW SUPPLIED

BENICAR HCT® is supplied as 20 mg/12.5 mg: reddish-yellow, circular, film-coated tablets, approximately 8.5 mm in diameter, with "Sankyo" debossed on one side and “C22” on the other side. Each tablet contains 20 mg of olmesartan medoxomil and 12.5 mg of hydrochlorothiazide.

40 mg/12.5 mg: reddish-yellow, oval, film-coated tablets, approximately 15 x 7 mm, with "Sankyo" debossed on one side and “C23” on the other side. Each tablet contains 40 mg of olmesartan medoxomil and 12.5 mg of hydrochlorothiazide.

40 mg/25 mg: pink, oval, film-coated tablets, approximately 15 x 7 mm, with "Sankyo" debossed on one side and "C25" on the other side. Each tablet contains 40 mg of olmesartan medoxomil and 25 mg of hydrochlorothiazide.

Tablets are supplied as follows:

 | 20 mg/12.5 mg | 40 mg/12.5 mg | 40 mg/25 mg
Bottle of 30 tablets | NDC 54868-5170-0 | NDC 54868-5075-0 | NDC 54868-5078-0
Bottle of 90 tablets | NDC 54868-5170-1 | NDC 54868-5075-1 | NDC 54868-5078-1

Storage

Store at 20-25°C (68-77°F) [See USP Controlled Room Temperature].

Manufactured for Daiichi Sankyo, Inc., Parsippany, NJ 07054

Rx Only

Copyright © Daiichi Sankyo, Inc. 2006. All rights reserved.

P1800706 Rev. December 2006

Relabeling and Repackaging by:
Physicians Total Care, Inc.
Tulsa, OK 74146

PRINCIPAL DISPLAY PANEL

BENICAR HCT®

20 mg/12.5 mg

40 mg/12.5 mg

40 mg/25 mg